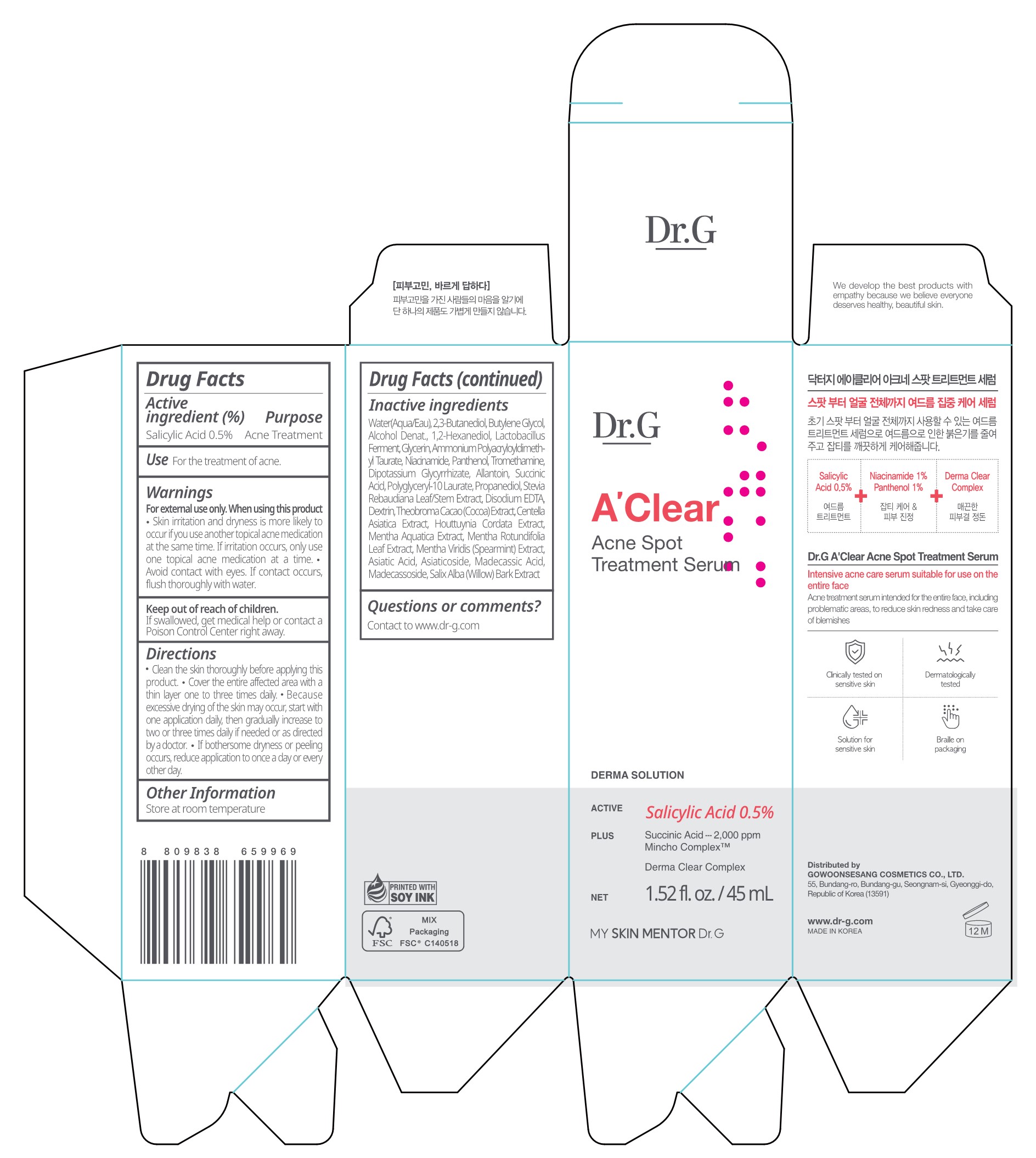 DRUG LABEL: Dr.G A CLEAR ACNE SPOT TREATMENT SERUM
NDC: 51621-412 | Form: LIQUID
Manufacturer: GOWOONSESANG COSMETICS CO., LTD.
Category: otc | Type: HUMAN OTC DRUG LABEL
Date: 20250320

ACTIVE INGREDIENTS: SALICYLIC ACID 0.5 g/100 mL
INACTIVE INGREDIENTS: GLYCERIN; SUCCINIC ACID; STEVIA REBAUDIUNA LEAF; BUTYLENE GLYCOL; CENTELLA ASIATICA TRITERPENOIDS; COCOA; ALLANTOIN; HOUTTUYNIA CORDATA FLOWERING TOP; ALCOHOL; 1,2-HEXANEDIOL; POLYGLYCERYL-10 LAURATE; MADECASSOSIDE; DEXTRIN, CORN; PANTHENOL; PROPANEDIOL; AMMONIUM POLYACRYLOYLDIMETHYL TAURATE; NIACINAMIDE; ASIATIC ACID; TROMETHAMINE; SALIX ALBA BARK; MENTHA X ROTUNDIFOLIA LEAF; DIPOTASSIUM GLYCYRRHIZATE; MADECASSIC ACID; WATER; 2,3-BUTANEDIOL; EDETATE DISODIUM; MENTHA SPICATA; ASIATICOSIDE

Active ingredient

Salicylic Acid 0.5%

Purpose

Acne Treatment

Use

For the treatment of acne.

Warnings

For external use only. When using this product

- Skin irritation and dryness is more likely to occur if you use another topical acne medication at the same time. If irritation occurs, only use one topical acne medication at a time .
- Avoid contact with eyes. If contact occurs, flush thoroughly with water.

Keep out of reach of children.

If swallowed, get medical help or contact a Poison Control Center right away.

Directions

- Clean the skin thoroughly before applying this product.
- Cover the entire affected area with a thin layer one to three times daily.
- Because excessive drying of the skin may occur, start with one application daily, then gradually increase to two or three times daily if needed or as directed by a doctor.
- If bothersome dryness or peeling occurs, reduce application to once a day or every other day.

Other Information

Store at room temperature

Inactive ingredients

Water(Aqua/Eau), 2,3-Butanediol, Butylene Glycol, Alcohol Denat., 1,2-Hexanediol, Lactobacillus Ferment, Glycerin, Ammonium Polyacryloyldimeth yl Taurate, Niacinamide, Panthenol, Tromethamine, Dipotassium Glycyrrhizate, Allantoin, Succinic Acid, Polyglyceryl-10 Laurate, Propanediol, Stevia Rebaudiana Leaf/Stem Extract, Disodium EDTA, Dextrin, Theobroma Cacao (Cocoa) Extract, Centella Asiatica Extract, Houttuynia Cordata Extract, Mentha Aquatica Extract, Mentha Rotundifolia Leaf Extract, Mentha Viridis (Spearmint) Extract, Asiatic Acid, Asiaticoside, Madecassic Acid, Madecassoside, Salix Alba (Willow) Bark Extract

Questions or comments?

Contact to www.dr-g.com